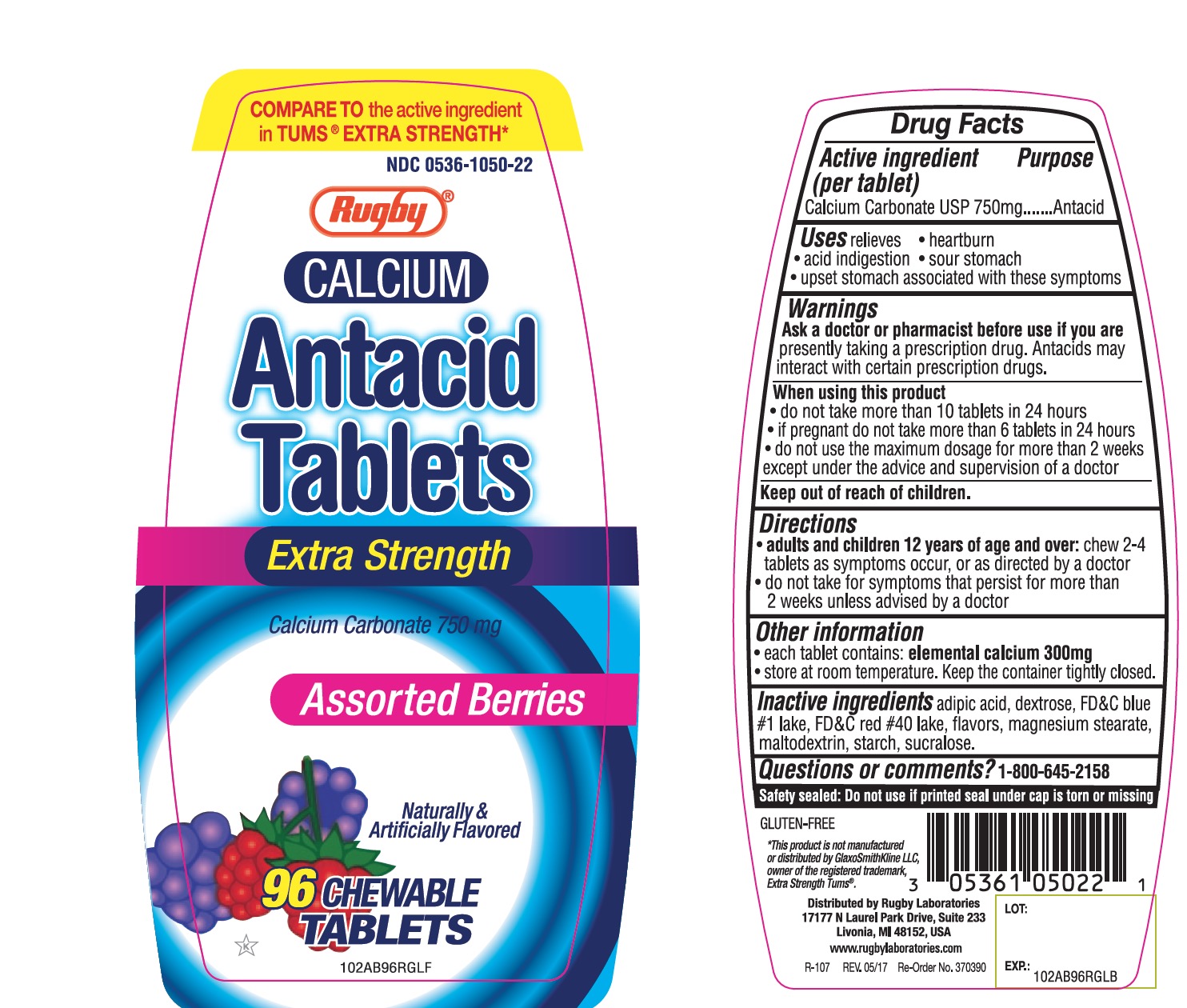 DRUG LABEL: Rugby

NDC: 0536-1050 | Form: TABLET, CHEWABLE
Manufacturer: Rugby Laboratories
Category: otc | Type: HUMAN OTC DRUG LABEL
Date: 20251025

ACTIVE INGREDIENTS: CALCIUM CARBONATE 750 mg/1 1
INACTIVE INGREDIENTS: ADIPIC ACID; DEXTROSE, UNSPECIFIED FORM; FD&C BLUE NO. 1; FD&C RED NO. 40; MAGNESIUM STEARATE; MALTODEXTRIN; STARCH, CORN; SUCRALOSE

Drug Facts

Active ingredient (per tablet)

Calcium Carbonate USP 750mg

Purpose

Antacid

Uses

relieves:

- heartburn
- acid indigestion
- sour stomach
- upset stomach associated with these symptoms

Warnings

Ask a doctor or pharmacist before use if you are presently taking a prescription drug. Antacids may interact with certain prescription drugs.

When using this product

- do not take more than 10 tablets in 24 hours
- if pregnant do not take more than 6 tablets in 24 hours
- do not use the maximum dosage for more than 2 weeks except under the advice and supervision of a doctor

Directions

- adults and children 12 years of age and over:chew 2-4 tablets as symptoms occur, or as directed by a doctor.
- do not take for symptoms that persist for more than 2 weeks unless advised by a doctor

Other Information

- each tablet contains : elemental calcium 300mg
- Store at room temperature. Keep the container tightly closed.

Inactive ingredients

adipic acid , dextrose, FD&C blue#1 lake, FD&C red#40 lake, flavors, magnesium stearate, maltodextrin, starch, sucralose.

Question or comments?

1-800-645-2158

Safety sealed: Do not use if printed seal under cap is torn or missing

Package/Label Principal Display Panel

COMPARE TO the active ingredient in TUMS® EXTRA STRENGTH

NDC 0536-1050-22

Rugby

CALCIUM

Antacid

Tablets

Extra Strength

Calcium Carbonate 750mg

Assorted Berries

Naturally & Artificially Flavored

96 Chewable Tablets

GLUTEN-FREE

*This product is not manufactured or distributed by GlaxoSmithKline LLC,

Owner of the registered trademark, Extra Strength Tums®

Distributed by Rugby Laboratories

17177 N Laurel Park Drive, Suite 233

Livonia, MI 48150, USA

www.rugbylaboratories.com